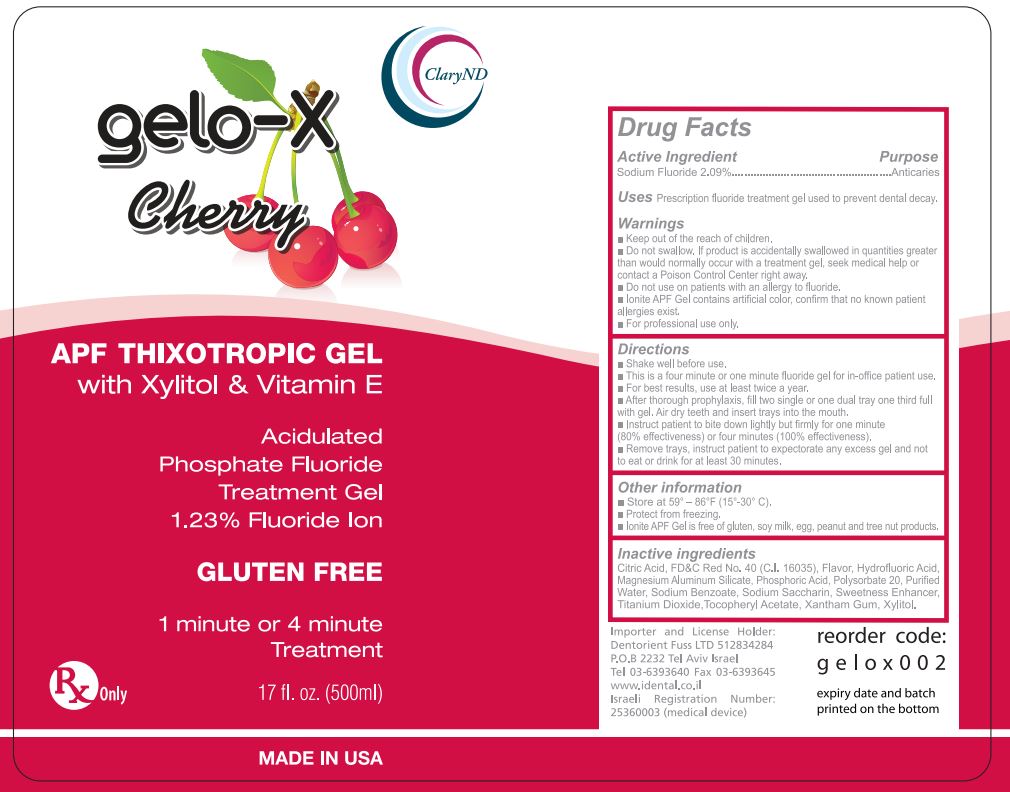 DRUG LABEL: gelo-X
NDC: 53045-209 | Form: GEL, DENTIFRICE
Manufacturer: Dharma Research, Inc.
Category: prescription | Type: HUMAN PRESCRIPTION DRUG LABEL
Date: 20210630

ACTIVE INGREDIENTS: SODIUM FLUORIDE 10.241 g/100 g
INACTIVE INGREDIENTS: CITRIC ACID ISOPROPYL ETHER; FD&C RED NO. 40; MAGNESIUM ALUMINUM SILICATE; PHOSPHORIC ACID; POLYSORBATE 20; WATER; SODIUM BENZOATE; SACCHARIN SODIUM; TITANIUM DIOXIDE; .ALPHA.-TOCOPHEROL ACETATE; XANTHAN GUM; XYLITOL

Storage and Handling

- Store at 59° – 86° F (15° – 30° C)
- Protect from freezing
- Product is free of gluten, soy milk, egg, peanut, and tree nut products

Inactive Ingredients

Citric acid, FD&C Red No. 40 (C.I. 16035), Flavor, Hydrofluoric Acid, Magnesium Aluminum Silicate, Phosphoric Acid, Polysorbate 20, Purified Water, Sodium Benzoate, Sodium Saccharine, Sweetness enhancer, Titanium dioxide, Tocopherol acetate, Xanthan gum, Xylitol

Warnings and Precautions

•Keep out of reach of children

•Do not swallow. If product is accidentally swallowed in quantities greater than would normally occur with a treatment gel, seek medical help or contact a Poison Control Center right away

•Do not use on patients with an allergy to fluoride

•Product contains artificial color; confirm that no known patient allergies exist

•For professional use only

Instructions for Use

•Shake well before use
•This is a four minute or one minute fluoride gel for in-office patient use.
•For best results, use at least twice per year
•After thorough prophylaxis, fill two single or one dual tray one third full with gel. Air dry teeth and insert trays into mouth.
•Instruct patient to bite down lightly but firmly for one minute (80% effectiveness) or four minutes (100% effectiveness)
•Remove trays, instruct patient to expectorate any excess gel and not to eat or drink for at least 30 minutes